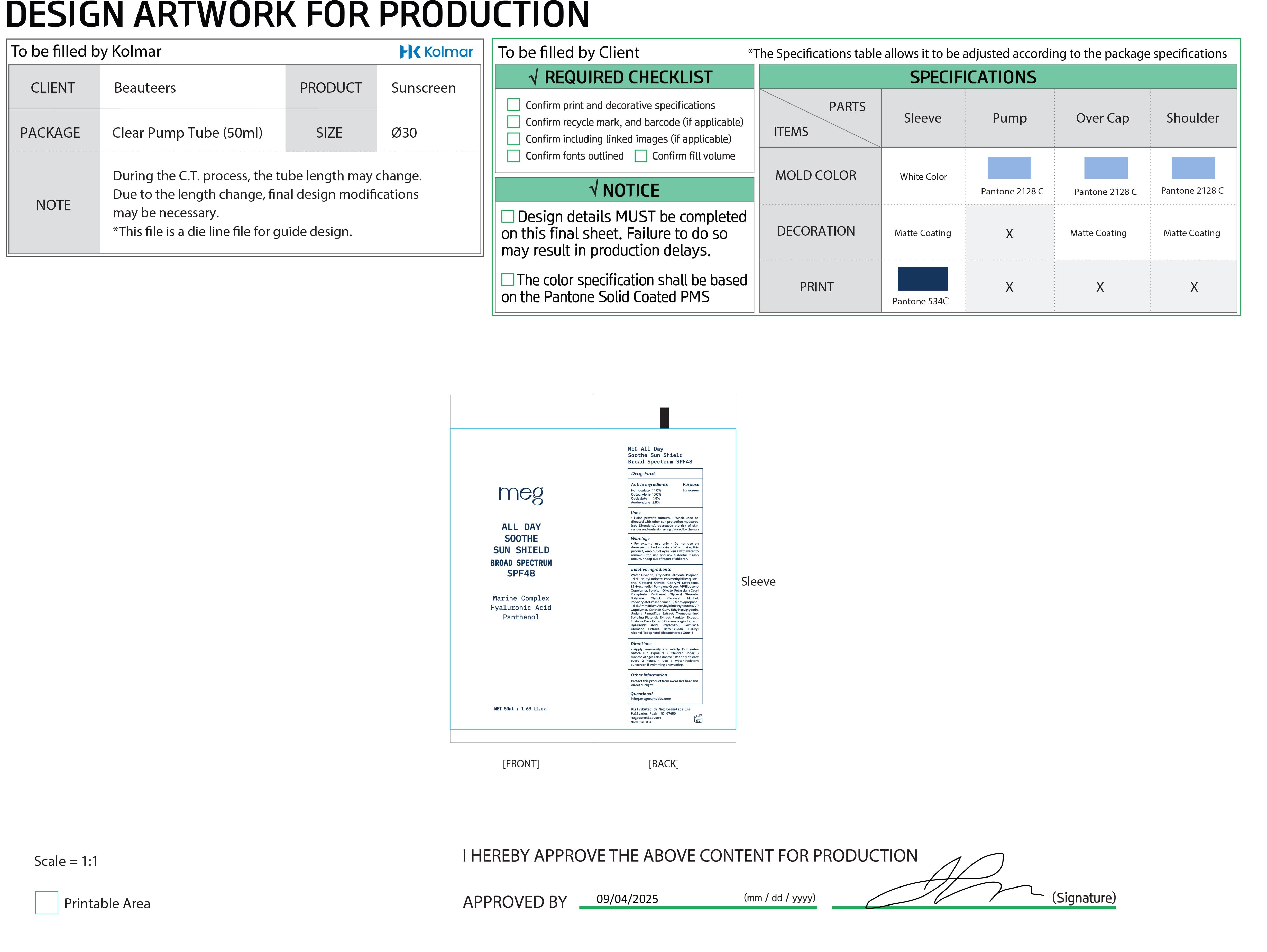 DRUG LABEL: meg
NDC: 87225-001 | Form: CREAM
Manufacturer: Meg Cosmetics Inc
Category: otc | Type: HUMAN OTC DRUG LABEL
Date: 20251216

ACTIVE INGREDIENTS: OCTISALATE 45 mg/1 g; OCTOCRYLENE 100 mg/1 g; HOMOSALATE 140 mg/1 g; AVOBENZONE 28 mg/1 g
INACTIVE INGREDIENTS: BUTYLOCTYL SALICYLATE; ETHYLHEXYLGLYCERIN; TROMETHAMINE; ECKLONIA CAVA; HYALURONIC ACID; AMMONIUM ACRYLOYLDIMETHYLTAURATE/VP COPOLYMER; XANTHAN GUM; VINYLPYRROLIDONE/EICOSENE COPOLYMER; POLYETHER-1 (2800 MPA.S); PORTULACA OLERACEA WHOLE; T-BUTYL ALCOHOL; PANTHENOL; METHYLPROPANEDIOL; CODIUM FRAGILE; BUTYLENE GLYCOL; CETEARYL ALCOHOL; POLYACRYLATE CROSSPOLYMER-6; PROPANEDIOL; DIBUTYL ADIPATE; GLYCERYL STEARATE; UNDARIA PINNATIFIDA; TOCOPHEROL; BIOSACCHARIDE GUM-1; SPIRULINA PLATENSIS; PENTYLENE GLYCOL; WATER; SORBITAN OLIVATE; CETEARYL OLIVATE; CAPRYLYL METHICONE; 1,2-HEXANEDIOL; GLYCERIN; POLYMETHYLSILSESQUIOXANE (4.5 MICRONS); POTASSIUM CETYL PHOSPHATE

DOSAGE AND ADMINISTRATION

- Apply generously and evenly 15 minutes before sun exposure.
- Children under 6 months of age: Ask a doctor.
- Reapply at least every 2 hours.
- Use a water-resistant sunscreen if swimming or sweating.

INACTIVE INGREDIENT

Water (Aqua)
Glycerin
Butyloctyl Salicylate
Propanediol
Dibutyl Adipate
Polymethylsilsesquioxane
Cetearyl Olivate
Caprylyl Methicone
1,2-Hexanediol
Pentylene Glycol
VP/Eicosene Copolymer
Sorbitan Olivate
Potassium Cetyl Phosphate
Panthenol
Glyceryl Stearate
Butylene Glycol
Cetearyl Alcohol
Polyacrylate Crosspolymer-6
Methylpropanediol
Ammonium Acryloyldimethyltaurate/VP Copolymer
Xanthan Gum
Ethylhexylglycerin
Undaria Pinnatifida Extract
Tromethamine
Spirulina Platensis Extract
Plankton Extract
Ecklonia Cava Extract
Codium Fragile Extract
Hyaluronic Acid
Polyether-1
Portulaca Oleracea Extract
Beta-Glucan
T-Butyl Alcohol
Tocopherol
Biosaccharide Gum-1

INDICATIONS AND USAGE

- Helps prevent sunburn
- When used as directed with other sun protection measures (see Directions), decreases the risk of skin cancer and early skin aging caused by the sun.

ACTIVE INGREDIENT

Homosalate 14.00%
Octocrylene 10.00%
Octisalate 4.50%
Avobenzone 2.80%

DO NOT USE

No “Do not use” statements apply for this product when used as directed.

WARNINGS

- For external use only.
- Do not use on damaged or broken skin.
- When using this product, keep out of eyes. Rinse with water to remove.
- Stop use and ask a doctor if rash occurs.
- Keep out of reach of children.

PURPOSE

Sunscreen

Keep out of reach of children.
If swallowed, get medical help or contact a Poison Control Center right away.

PACKAGE LABEL

Image of immediate container labeling (inner tube), 50 mL, NDC 87225-001-01